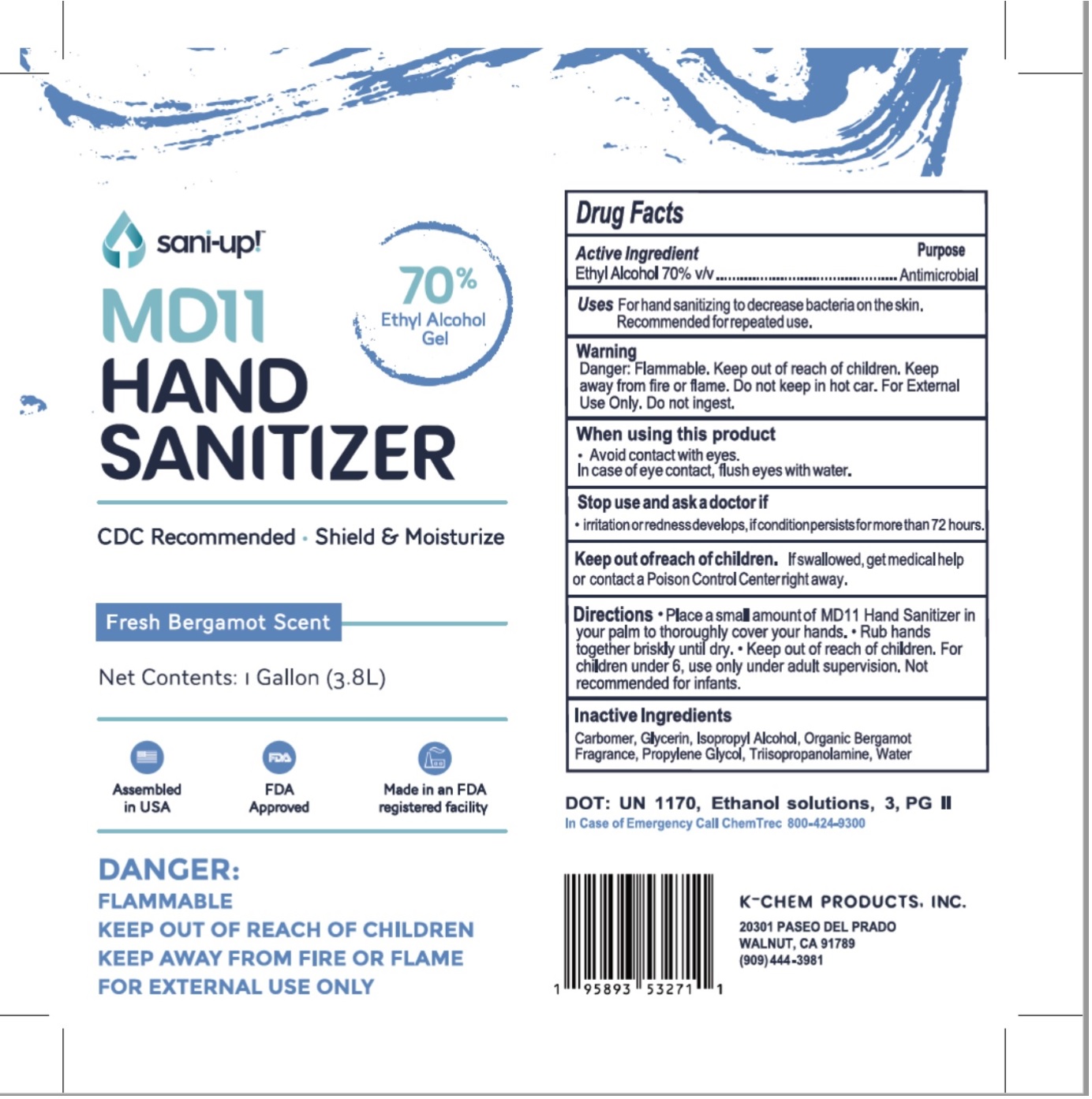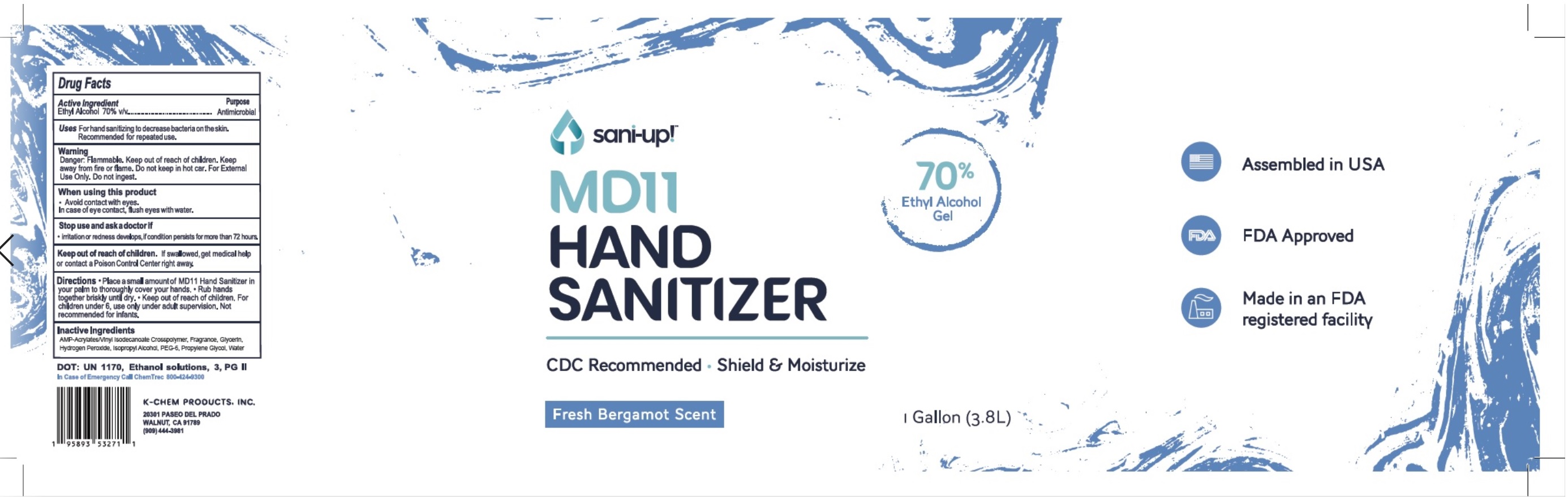 DRUG LABEL: MD11 Hand Sanitizer
NDC: 80298-001 | Form: LIQUID
Manufacturer: K-Chem Products, Inc
Category: otc | Type: HUMAN OTC DRUG LABEL
Date: 20210111

ACTIVE INGREDIENTS: ALCOHOL 0.7 L/1 L
INACTIVE INGREDIENTS: HYDROGEN PEROXIDE; GLYCERIN; ISOPROPYL ALCOHOL; PROPYLENE GLYCOL; WATER

MD11 Hand Sanitizer

ACTIVE INGREDIENT

Ethyl Alcohol ...........70.0% v/v

Purpose

Antiseptic

Uses

For hand sanitizing to decrease bacteria on the skin.

recommended for repeated use.

Warnings

Danger: Flammable. Keep out of Reach of children. Keep away from fire or flame. Do not keep in hot car. For external use only. Do not ingest.

When Using this Product

- Avoid contact with eyes.

- In case of eye contact, flush eyes with water.

Stop use and ask a doctor if

-Irritation or redness develops, if condition persists for more than 72 hours.

Keep out of reach of children. If swallowed, get medical help

or contact a Poison Control Center immediately.

Directions

-Pump a small amount of MD11 Hand Sanitizer in your palm to thoroughly cover your hands.

-Rub hands together brisky until dry

-Keep out of reach of children

-For children under 6, use only under adult supervision.

-Not recommended for infants.

Inactive Ingredients

AMP-Acrylates/Vinyl Isodecanoate Crosspolymer, Fragrance, Glycerin, Hydrogen Peroxide, Isopropyl Alcohol, PEG-6, Propylene Glycol, Water.

MD11 Hand Sanitizer

Fresh Bergamot Scent

1 Gallon 3.8L

4x1 Gallon Box